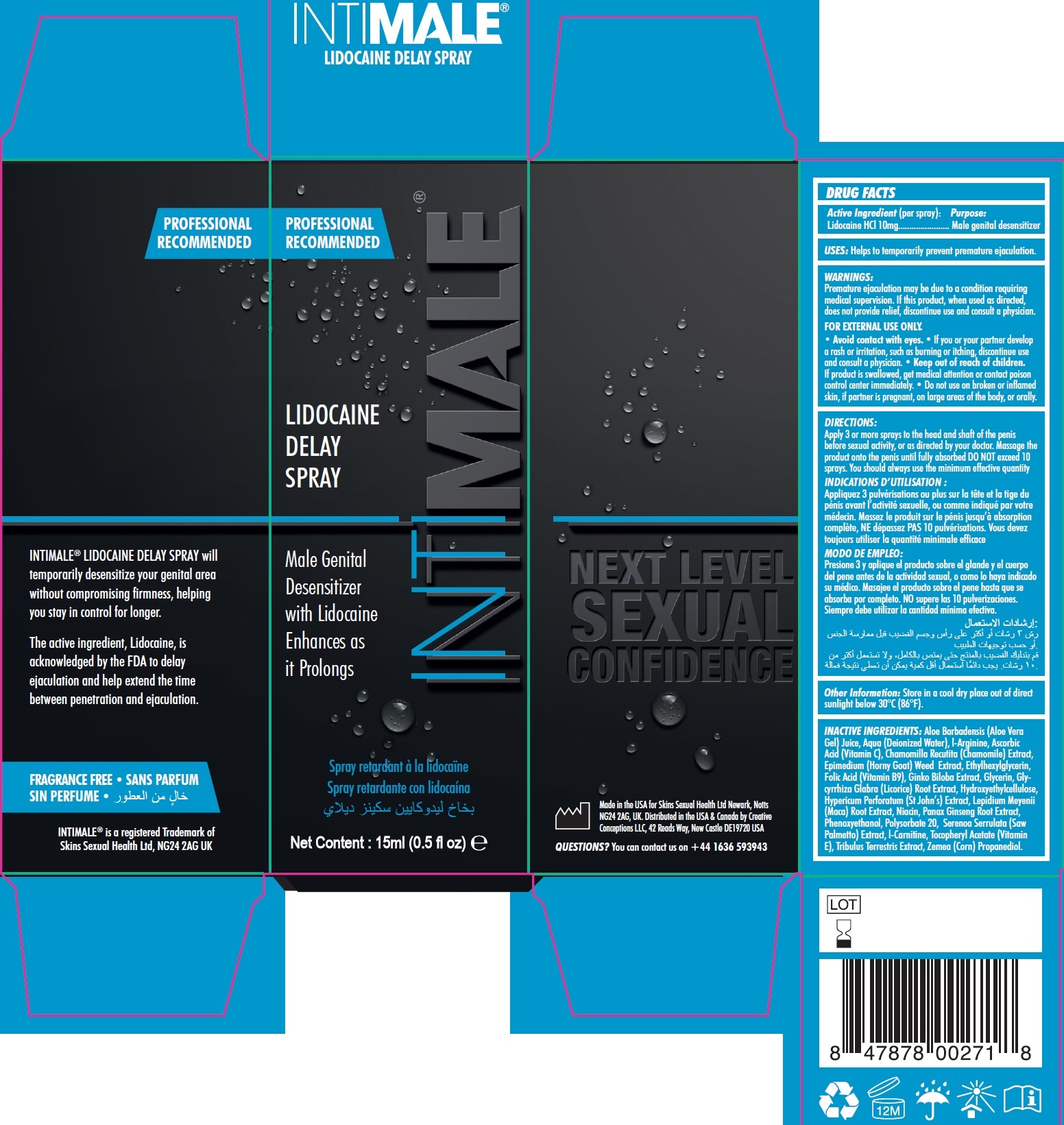 DRUG LABEL: INTIMALE LIDOCAINE DELAY
NDC: 81923-368 | Form: SOLUTION
Manufacturer: SKINS SEXUAL HEALTH LIMITED
Category: otc | Type: HUMAN OTC DRUG LABEL
Date: 20250128

ACTIVE INGREDIENTS: LIDOCAINE HYDROCHLORIDE 10 mg/1 mL
INACTIVE INGREDIENTS: ALOE VERA LEAF; WATER; ARGININE; ASCORBIC ACID; CHAMOMILE; ETHYLHEXYLGLYCERIN; FOLIC ACID; GLYCERIN; GLYCYRRHIZA GLABRA; HYDROXYETHYL CELLULOSE, UNSPECIFIED; HYPERICUM PERFORATUM WHOLE; LEPIDIUM MEYENII ROOT; NIACIN; ASIAN GINSENG; PHENOXYETHANOL; POLYSORBATE 20; SAW PALMETTO; LEVOCARNITINE; .ALPHA.-TOCOPHEROL ACETATE; TRIBULUS TERRESTRIS WHOLE; CORN

INTIMALE LIDOCAINE DELAY SPRAY

Active Ingredient (per spray):

Lidocaine HCL 10mg

Purpose:

Male genital desensitizer

USES:

Helps to temporarily prevent premature ejaculation.

WARNINGS:

• Premature ejaculation may be due to a condition requiring medical supervision. If this product, when used as directed, does not provide relief, discontinue use and consult a physician. • • • If you or your partner develop a rash or irritation, such as burning or itching, discontinue use and consult a physician.
FOR EXTERNAL USE ONLY. Avoid contact with eyes.

Keep out of reach of children.

• If product is swallowed, get medical attention or contact poison control center immediately.

Do not use

• on broken or inflamed skin, if partner is pregnant, on large areas of the body, or orally.

DIRECTIONS:

Apply 3 or more sprays to the head and shaft of the penis before sexual activity, or as directed by your doctor. Massage the product onto the penis until fully absorbed DO NOT exceed 10 sprays. You should always use the minimum effective quantity

Other Information:

Store in a cool dry place out of direct sunlight below 30°C (86°F).

INACTIVE INGREDIENTS:

Aloe Barbadensis (Aloe Vera Gel) Juice, Aqua (Deionized Water), l-Arginine, Ascorbic Acid (Vitamin C), Chamomilla Recutita (Chamomile) Extract, Epimedium (Horny Goat) Weed Extract, Ethylhexylglycerin, Folic Acid (Vitamin B9), Ginko Biloba Extract, Glycerin, Glycyrrhiza Glabra (Licorice) Root Extract, Hydroxyethylcellulose, Hypericum Perforatum (St John’s) Extract, Lepidium Meyenii (Maca) Root Extract, Niacin, Panax Ginseng Root Extract, Phenoxyethanol, Polysorbate 20, Serenoa Serrulata (Saw Palmetto) Extract, l-Carnitine, Tocopheryl Acetate (Vitamin E), Tribulus Terrestris Extract, Zemea (Corn) Propanediol.

QUESTIONS?

You can contact us on +44 1636 593943